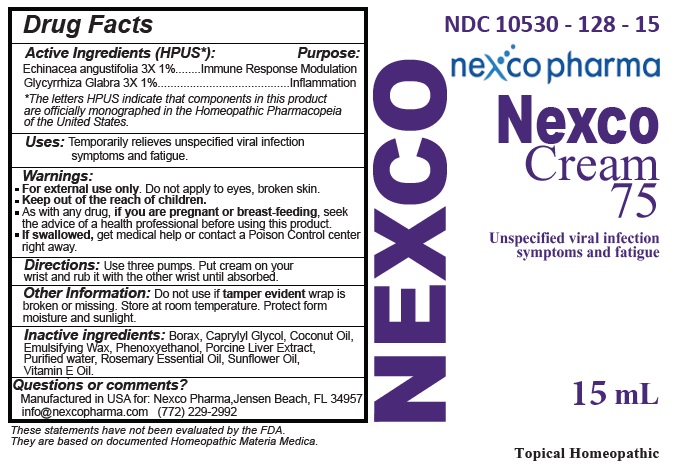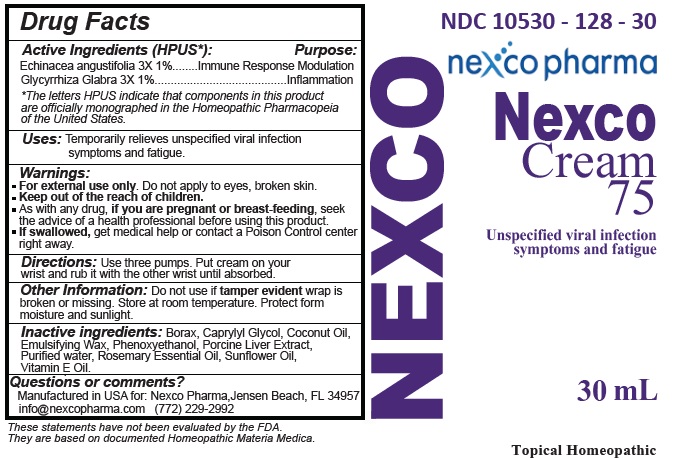 DRUG LABEL: Nexco Cream 75
NDC: 10530-128 | Form: CREAM
Manufacturer: Nexco Pharma
Category: homeopathic | Type: HUMAN OTC DRUG LABEL
Date: 20191113

ACTIVE INGREDIENTS: ECHINACEA ANGUSTIFOLIA 3 [hp_X]/1 mL; GLYCYRRHIZA GLABRA 3 [hp_X]/1 mL
INACTIVE INGREDIENTS: SODIUM BORATE; CAPRYLYL GLYCOL; COCONUT OIL; POLYSORBATE 60; PHENOXYETHANOL; PORK LIVER; WATER; ROSEMARY OIL; SUNFLOWER OIL; .ALPHA.-TOCOPHEROL

Nexco Cream 75

Active Ingredients (HPUS*): Purpose:

Echinacea angustifolia 3X 1% ........ Immune Response Modulation

Glycyrrhiza Glabra 3X 1% .......................................... Inflammation

* The letters HPUS indicate that components in this product are officially monographed in the Homeopathic Pharmacopeia of the United States.

Purpose:

Immune Response Modulation

Inflammation

INDICATIONS AND USAGE

Uses: Temporarily relieves unspecified viral infection symptoms and fatigue.

These statements have not been evaluated by the FDA.

They are based on documented Homeopathic Materia Medica.

Warnings:

- For external use only. Do not apply to eyes, broken skin.
- As with any drug, if you are pregnant or breast-feeding, seek the advice of a health professional before using this product.
- If swallowed, get medical help or contact a Poison Control center right away.

- Keep out of the reach of children.

DOSAGE AND ADMINISTRATION

Directions: Use three pumps. Put cream on your wrist and rub it with the other wrist until absorbed.

Other Information: Do not use if tamper evident wrap is broken or missing. Store at room temperature. Protect from moisture and sunlight.

INACTIVE INGREDIENT

Inactive ingredients: Borax, Caprylyl Glycol, Coconut Oil, Emulsifying Wax, Phenoxyethanol, Porcine Liver Extract, Purified water, Rosemary Essential Oil, Sunflower Oil, Vitamin E Oil.

Questions or comments?

Manufactured in USA for: Nexco Pharma, Jensen Beach, FL 34957

info@nexcopharma.com (772) 229-2992

PACKAGE LABEL

NDC 10530-128-15 \10530-128-30

nexco pharma

Nexco Cream 75

Unspecified viral infection

symptoms and fatigue

15 mL\ 30 mL

Topical Homeopathic